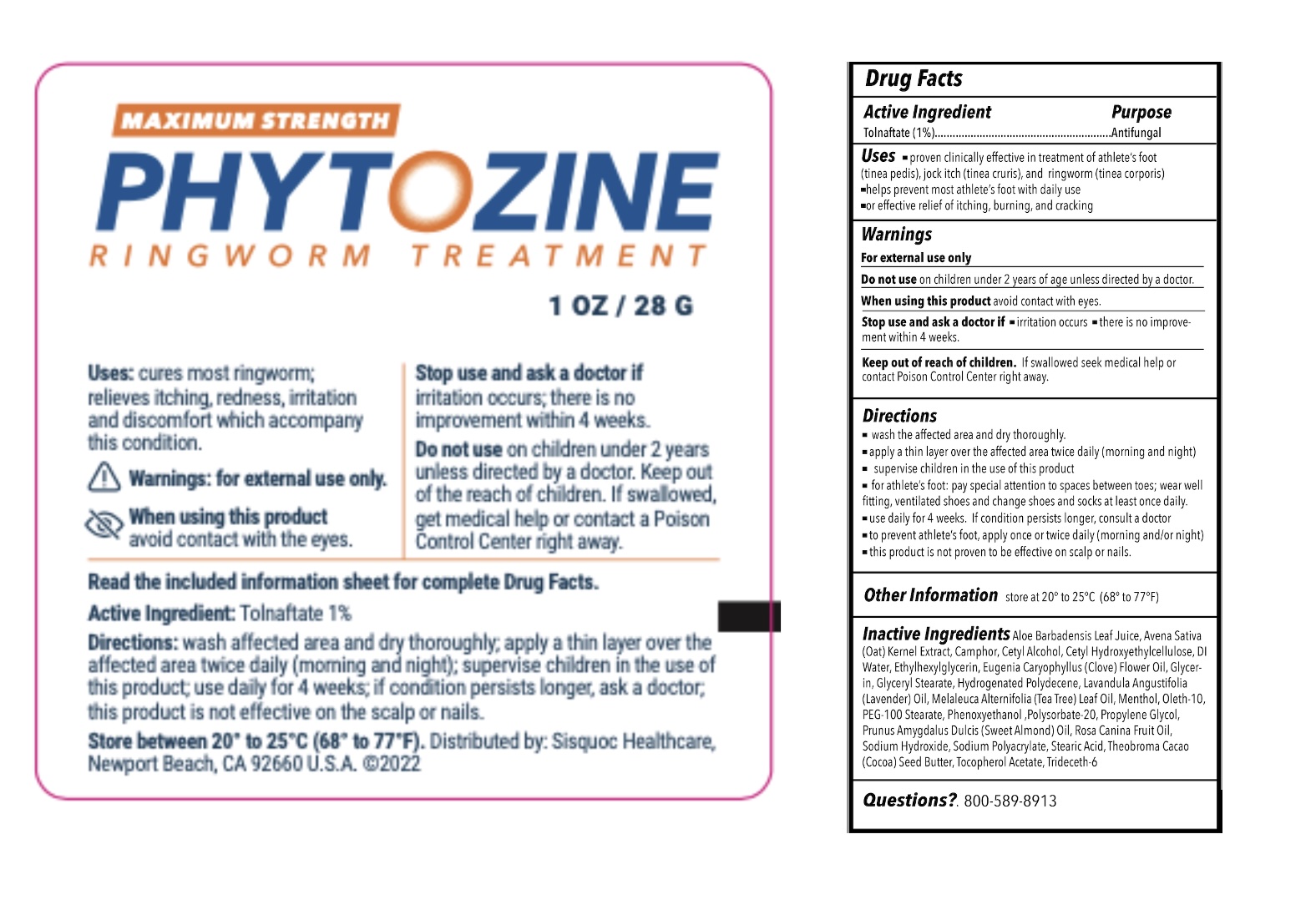 DRUG LABEL: PHYTOZINE RINGWORM TREATMENT
NDC: 71229-101 | Form: OINTMENT
Manufacturer: The Sisquoc Healthcare Corporation
Category: otc | Type: HUMAN OTC DRUG LABEL
Date: 20250421

ACTIVE INGREDIENTS: TOLNAFTATE 1 g/100 g
INACTIVE INGREDIENTS: WATER; ALMOND OIL; POLYSORBATE 20; SODIUM POLYACRYLATE (8000 MW); HYDROGENATED POLYDECENE (550 MW); TRIDECETH-6; GLYCERYL MONOSTEARATE; PEG-100 STEARATE; PROPYLENE GLYCOL; CETYL ALCOHOL; OLETH-10 PHOSPHATE; GLYCERIN; OAT; ALOE VERA LEAF; ARCTOSTAPHYLOS UVA-URSI LEAF; PROPOLIS WAX; THEOBROMA CACAO WHOLE; ROSA CANINA FRUIT OIL; CAMPHOR (SYNTHETIC); MENTHOL; MELALEUCA ALTERNIFOLIA LEAF; LAVANDULA ANGUSTIFOLIA WHOLE; JASMINUM OFFICINALE WHOLE; CLOVE LEAF OIL; .ALPHA.-TOCOPHEROL ACETATE; STEARIC ACID; BUTYLENE GLYCOL; CETYL HYDROXYETHYLCELLULOSE (350000 MW); SODIUM HYDROXIDE; PHENOXYETHANOL; ETHYLHEXYLGLYCERIN

Sisquoc HC (as PLD) - PHYTOZINE RINGWORM TREATMENT (71229-101)

ACTIVE INGREDIENT

TOLNAFTATE 1%

PURPOSE

ANTIFUNGAL

USES

- CURES MOST RINGWORM
- RELIEVES ITCHING, REDNESS, IRRITATION AND DISCOMFORT WHICH ACCOMPANY THIS CONDITION.

WARNINGS

FOR EXTERNAL USE ONLY.

WHEN USING THIS PRODUCT AVOID CONTACT WITH THE EYES.

STOP USE AND ASK A DOCTOR IF

- IRRITATION OCCURS
- THERE IS NO IMPROVEMENT WITHIN 4 WEEKS.

DO NOT USE ON CHILDREN UNDER 2 YEARS OF AGE UNLESS DIRECTED BY A DOCTOR.

KEEP OUT OF REACH OF CHILDREN. IF SWALLOWED, GET MEDICAL HELP OR CONTACT A POISON CONTROL CENTER RIGHT AWAY.

DIRECTIONS

- For the cure of most ringworm (tinea corporis) and athlete’s foot (tinea pedis). For relief of itching, scaling, cracking, burning, redness, soreness, irritation and discomforts which may accompany these conditions.
- Wash affected area and dry thoroughly. Apply a layer of PHYTOZINE over the affected area twice daily (morning and night). Allow the cream to dry for at least 3 minutes before covering the affectedarea with clothing.
- Wash hands after each application to preventthe chance of the infection spreading to other parts of the skin.
- Most ringworm infections will require between 3-4 weeks of continuous daily treatment before the infection is completely eliminated.
- Proper use of PHYTOZINE will eliminate most ringworm infections. If the condition persists longer, contact a physician or medical professional.

INACTIVE INGREDIENTS

Water, Prunus Amygdalus Dulcis (Sweet Almond) Oil, Polysorbate-20, Sodium Polyacrylate, Hydrogenated Polydecene, Trideceth-6, Glyceryl Stearate, PEG-100, Stearate, Propylene Glycol, Cetyl Alcohol, Oleth-10 Phosphate, Glycerin, Avena (Oat), Kernel Extract, Aloe Barbadensis Leaf Juice, Actrostaphylos Uva Ursi Leaf Extract, Propolis Extract, Theobroma Cacao
(Cocoa) Seed Butter, Rosa Canina Fruit Oil, Camphor, Menthol, Melaleuca Alternifolia (Tea Tree) Leaf Oil, Lavandula
Angustifolia (Lavender) Oil, Jasminum Officinale (Jasmine) Oil, Eugenia Caryophyllus (Clove) Leaf Oil, Tocopheryl
Acetate, Stearic Acid, Propylene Glycol, Butylene Glycol, Cetyl Hydroxyethylcellulose, Sodium Hydroxide, Phenoxyethanol , Ethylhexylglycerin

OTHER SAFETY INFORMATION

Store between 20°c to 25°C (68° to 77°F)